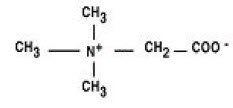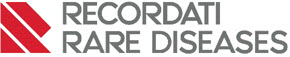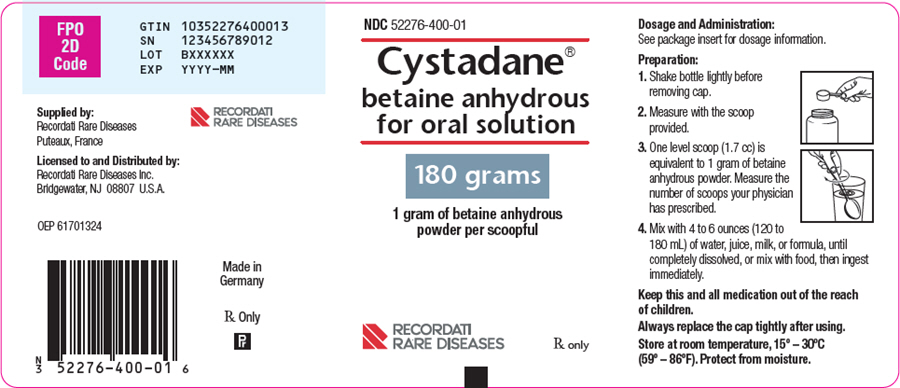 DRUG LABEL: Cystadane
NDC: 52276-400 | Form: POWDER, FOR SOLUTION
Manufacturer: Recordati Rare Diseases
Category: prescription | Type: HUMAN PRESCRIPTION DRUG LABEL
Date: 20250630

ACTIVE INGREDIENTS: BETAINE 1 g/1 g

HIGHLIGHTS OF PRESCRIBING INFORMATION

These highlights do not include all the information needed to use CYSTADANE safely and effectively. See full prescribing information for CYSTADANE.
CYSTADANE ® (betaine anhydrous for oral solution)
Initial U.S. Approval: 1996

1 INDICATIONS AND USAGE

CYSTADANE is a methylating agent indicated in pediatric and adult patients for the treatment of homocystinuria to decrease elevated homocysteine blood concentrations. Included within the category of homocystinuria are (1):

- Cystathionine beta-synthase (CBS) deficiency
- 5,10-methylenetetrahydrofolate reductase (MTHFR) deficiency
- Cobalamin cofactor metabolism (cbl) defect

2 DOSAGE AND ADMINISTRATION

Adults and Pediatric Patients 3 Years of Age and Older

- The recommended dosage is 6 grams per day, administered orally in divided doses of 3 grams twice daily. (2.1)

Pediatric Patients Less than 3 Years of Age

- The recommended starting dosage is 100 mg/kg/day, administered orally in divided doses of 50 mg/kg twice daily, and then increased weekly by 50 mg/kg increments. (2.1)
- Monitor patient response by plasma homocysteine concentrations. (2.1)
- Increase the dosage gradually until the plasma total homocysteine concentration is undetectable or present only in small amounts. (2.1)

Preparation and Administration Instructions

- Prescribed amount of CYSTADANE should be measured with the measuring scoop provided and then dissolved in 4 to 6 ounces of water, juice, milk, or formula until completely dissolved, or mixed with food for immediate ingestion. (2.2)

3 DOSAGE FORMS AND STRENGTHS

For oral solution: in bottles containing 180 grams of betaine anhydrous. (3)

4 CONTRAINDICATIONS

- None (4)

5 WARNINGS AND PRECAUTIONS

- Hypermethioninemia in Patients with CBS Deficiency:

CYSTADANE may worsen elevated plasma methionine concentrations and cerebral edema has been reported. Monitor plasma methionine concentrations in patients with CBS deficiency. Keep plasma methionine concentrations below 1,000 micromol/L through dietary modification and, if necessary, a reduction of CYSTADANE dosage. (5.1)

6 ADVERSE REACTIONS

Most common adverse reactions (> 2%) are: nausea and gastrointestinal distress, based on physician survey. (6.1)

To report SUSPECTED ADVERSE REACTIONS, contact Recordati Rare Diseases Inc. at 1-888-575-8344, or FDA at 1-800-FDA-1088 or www.fda.gov/medwatch.

FULL PRESCRIBING INFORMATION

1 INDICATIONS AND USAGE

CYSTADANE® is indicated for the treatment of homocystinuria to decrease elevated homocysteine blood concentrations in pediatric and adult patients. Included within the category of homocystinuria are:

- Cystathionine beta-synthase (CBS) deficiency
- 5,10-methylenetetrahydrofolate reductase (MTHFR) deficiency
- Cobalamin cofactor metabolism (cbl) defect

2 DOSAGE AND ADMINISTRATION

2.1 Dosage

Therapy with CYSTADANE should be directed by physicians knowledgeable in the management of patients with homocystinuria.

Adults and Pediatric Patients 3 Years of Age and Older

The recommended dosage is 6 grams per day, administered orally in divided doses of 3 grams twice daily.

Pediatric Patients Less than 3 Years of Age

The recommended starting dosage is 100 mg/kg/day divided in twice daily doses, and then increased weekly by 50 mg/kg increments.

Monitoring

Monitor patient response to CYSTADANE by homocysteine plasma concentration. Increase the dosage in all patients gradually until the plasma total homocysteine concentration is undetectable or present only in small amounts. An initial response in homocysteine plasma concentrations usually occurs within several days and steady state plasma concentrations occur within a month.

Monitor plasma methionine concentrations in patients with CBS deficiency [See Warnings and Precautions (5.1)].

Maximum Dosage

Dosages of up to 20 grams/day have been necessary to control homocysteine concentrations in some patients. However, one pharmacokinetic and pharmacodynamic in vitro simulation study indicated minimal benefit from exceeding a twice-daily dosing schedule and a 150 mg/kg/day dosage for CYSTADANE.

2.2 Preparation and Administration Instructions

- Shake bottle lightly before removing cap.
- Measure the number of scoops for the patient's dose with the scoop provided. One level scoop (1.7 mL) is equivalent to 1 gram of betaine anhydrous powder.
- Mix powder with 4 to 6 ounces (120 to 180 mL) of water, juice, milk, or formula until completely dissolved, or mix with food, then ingest mixture immediately.
- Always replace the cap tightly after using and protect the bottle from moisture.

3 DOSAGE FORMS AND STRENGTHS

CYSTADANE is a white, granular, hygroscopic powder for oral solution available in bottles containing 180 grams of betaine anhydrous.

4 CONTRAINDICATIONS

None.

5 WARNINGS AND PRECAUTIONS

5.1 Hypermethioninemia in Patients with CBS Deficiency

Patients with homocystinuria due to cystathionine beta-synthase (CBS) deficiency may also have elevated plasma methionine concentrations. Treatment with CYSTADANE may further increase methionine concentrations due to the remethylation of homocysteine to methionine. Cerebral edema has been reported in patients with hypermethioninemia, including patients treated with CYSTADANE [see Adverse Reactions (6.2)]. Monitor plasma methionine concentrations in patients with CBS deficiency. Plasma methionine concentrations should be kept below 1,000 micromol/L through dietary modification and, if necessary, a reduction of CYSTADANE dosage.

6 ADVERSE REACTIONS

The following serious adverse reactions are described elsewhere in labeling:

- Hypermethioninemia and cerebral edema in patients with CBS deficiency [see Warnings and Precautions (5.1)].

6.1 Clinical Trials Experience

Because clinical trials are conducted under widely varying conditions, adverse reaction rates observed in clinical trials of a drug cannot be directly compared to rates in the clinical trials of another drug and may not reflect the rates observed in practice.

The assessment of clinical adverse reactions is based on a survey study of 41 physicians, who treated a total of 111 homocystinuria patients with CYSTADANE. Adverse reactions were retrospectively recalled and were not collected systematically in this open-label, uncontrolled, physician survey. Thus, this list may not encompass all types of potential adverse reactions, reliably estimate their frequency, or establish a causal relationship to drug exposure. The following adverse reactions were reported (Table 1):

Table 1: Number of Patients with Adverse Reactions to CYSTADANE by Physician Survey
Adverse Reactions | Number of Patients
Nausea | 2
Gastrointestinal distress | 2
Diarrhea | 1
"Bad Taste" | 1
"Caused Odor" | 1
Questionable psychological changes | 1
"Aspirated the powder" | 1

6.2 Postmarketing Experience

The following adverse reactions have been identified during post approval use of CYSTADANE. Because these reactions are reported voluntarily from a population of uncertain size, it is not always possible to reliably estimate their frequency or establish a causal relationship to drug exposure.

Severe cerebral edema and hypermethioninemia have been reported within 2 weeks to 6 months of starting CYSTADANE therapy, with complete recovery after discontinuation of CYSTADANE. All patients who developed cerebral edema had homocystinuria due to CBS deficiency and had severe elevation in plasma methionine concentrations (range 1,000 to 3,000 microM). As cerebral edema has also been reported in patients with hypermethioninemia, secondary hypermethioninemia due to betaine therapy has been postulated as a possible mechanism of action [see Warnings and Precautions (5.1)].

Other adverse reactions include: anorexia, agitation, depression, irritability, personality disorder, sleep disturbed, dental disorders, diarrhea, glossitis, nausea, stomach discomfort, vomiting, hair loss, hives, skin odor abnormalities, and urinary incontinence.

8 USE IN SPECIFIC POPULATIONS

8.1 Pregnancy

Risk Summary

Available data from a limited number of published case reports and postmarketing experience with CYSTADANE use in pregnancy have not identified any drug associated risks for major birth defects, miscarriage, or adverse maternal or fetal outcomes. Animal reproduction studies have not been conducted with betaine.

The estimated background risk of major birth defects and miscarriage for the indicated population is unknown. All pregnancies have a background risk of birth defect, loss, or other adverse outcomes. In the U.S. general population, the estimated background risk of major birth defects and miscarriage in clinically recognized pregnancies is 2 to 4% and 15 to 20%, respectively.

8.2 Lactation

Risk Summary

There are no data on the presence of betaine in human or animal milk, the effects on the breastfed child, or the effects on milk production. The developmental and health benefits of breastfeeding should be considered along with the mother's clinical need for CYSTADANE and any potential adverse effects on the breastfed child from CYSTADANE or from the underlying maternal condition.

8.4 Pediatric Use

The safety and effectiveness of CYSTADANE have been established in pediatric patients. The majority of case studies of homocystinuria patients treated with CYSTADANE have been pediatric patients, including patients ranging in age from 24 days to 17 years [see Clinical Studies (14)]. Children younger than 3 years of age may benefit from dose titration [see Dosage and Administration (2.1)].

10 OVERDOSAGE

There is no information on CYSTADANE overdose in humans. In an acute toxicology study in rats, death occurred frequently at doses equal to or greater than 10 g/kg.

11 DESCRIPTION

CYSTADANE (betaine anhydrous for oral solution) is an agent for the treatment of homocystinuria. It contains no ingredients other than anhydrous betaine. CYSTADANE is a white, granular, hygroscopic powder, which is diluted in water and administered orally. The chemical name of betaine anhydrous powder is trimethylglycine. It has a molecular weight of 117.15. The structural formula is:

12 CLINICAL PHARMACOLOGY

12.1 Mechanism of Action

CYSTADANE acts as a methyl group donor in the remethylation of homocysteine to methionine in patients with homocystinuria. Betaine occurs naturally in the body. It is a metabolite of choline and is present in small amounts in foods such as beets, spinach, cereals, and seafood.

12.2 Pharmacodynamics

CYSTADANE was observed to lower plasma homocysteine concentrations in three types of homocystinuria, including CBS deficiency; MTHFR deficiency; and cbl defect. Patients have taken CYSTADANE for many years without evidence of tolerance. There has been no demonstrated correlation between Betaine concentrations and homocysteine concentrations.

In CBS-deficient patients, large increases in methionine concentrations over baseline have been observed. CYSTADANE has also been demonstrated to increase low plasma methionine and S-adenosylmethionine (SAM) concentrations in patients with MTHFR deficiency and cbl defect.

12.3 Pharmacokinetics

Pharmacokinetic studies of CYSTADANE are not available. Plasma betaine concentrations following administration of CYSTADANE have not been measured in patients and have not been correlated to homocysteine concentrations.

13 NONCLINICAL TOXICOLOGY

13.1 Carcinogenesis, Mutagenesis, Impairment of Fertility

Long-term carcinogenicity and fertility studies have not been conducted with CYSTADANE. No evidence of genotoxicity was demonstrated in the following tests: metaphase analysis of human lymphocytes; bacterial reverse mutation assay; and mouse micronucleus test.

14 CLINICAL STUDIES

CYSTADANE was studied in a double-blind, placebo-controlled, crossover study in 6 patients (3 males and 3 females) with CBS deficiency, ages 7 to 32 years at enrollment. CYSTADANE was administered at a dosage of 3 grams twice daily, for 12 months. Plasma homocystine concentrations were significantly reduced (p<0.01) compared to placebo. Plasma methionine concentrations were variable and not significantly different compared to placebo.

CYSTADANE has also been evaluated in observational studies without concurrent controls in patients with homocystinuria due to CBS deficiency, MTHFR deficiency, or cbl defect. A review of 16 case studies and the randomized controlled trial previously described was also conducted, and the data available for each study were summarized; however, no formal statistical analyses were performed. The studies included a total of 78 male and female patients with homocystinuria who were treated with CYSTADANE. This included 48 patients with CBS deficiency, 13 with MTHFR deficiency, and 11 with cbl defect, ranging in age from 24 days to 53 years. The majority of patients (n=48) received 6 gm/day, 3 patients received less than 6 gm/day, 12 patients received doses from 6 to 15 gm/day, and 5 patients received doses over 15 gm/day. Most patients were treated for more than 3 months (n=57) and 30 patients were treated for 1 year or longer (range 1 month to 11 years). Homocystine is formed nonenzymatically from two molecules of homocysteine, and both have been used to evaluate the effect of CYSTADANE in patients with homocystinuria. Plasma homocystine or homocysteine concentrations were reported numerically for 62 patients, and 61 of these patients showed decreases with CYSTADANE treatment. Homocystine decreased by 83 to 88% regardless of the pre-treatment concentration, and homocysteine decreased by 71 to 83%, regardless of the pre-treatment concentration. Clinical improvement, such as improvement in seizures, or behavioral and cognitive functioning, was reported by the treating physicians in about three-fourths of patients. Many of these patients were also taking other therapies such as vitamin B6 (pyridoxine), vitamin B12 (cobalamin), and folate with variable biochemical responses. In most cases, adding CYSTADANE resulted in a further reduction of either homocystine or homocysteine concentrations.

16 HOW SUPPLIED/STORAGE AND HANDLING

CYSTADANE is available in plastic bottles containing 180 grams of betaine anhydrous as a white, granular, hygroscopic powder. Each bottle is equipped with a plastic child-resistant cap and is supplied with a polypropylene measuring scoop. One level scoop (1.7 mL) is equal to 1 gram of betaine anhydrous powder.

NDC 52276-400-01 180 g/bottle

Storage

Store at room temperature, 15 to 30 ˚C (59 to 86 ˚F). Protect from moisture.

17 PATIENT COUNSELING INFORMATION

Preparation and Administration Instructions

Instruct patients and caregivers to administer CYSTADANE as follows:

- Shake bottle lightly before removing cap.
- Measure the number of scoops for the patient's dose with the scoop provided. One level scoop (1.7 mL) is equivalent to 1 gram of betaine anhydrous powder.
- Mix powder with 4 to 6 ounces (120 to 180 mL) of water, juice, milk, or formula until completely dissolved, or mix with food, then ingest mixture immediately.
- Always replace the cap tightly after using and protect bottle from moisture.

Supplied by:

Recordati Rare Diseases
Puteaux, France
Licensed to and Distributed by:

Recordati Rare Diseases Inc.
Bridgewater, NJ 08807 U.S.A.

For drug or ordering information please call AnovoRx Group, LLC, Customer service at 1-888-487-4703.

CYSTADANE® is a licensed trademark of Recordati Rare Diseases Inc.

This product label may have been updated. For the most recent prescribing information, please visit www.recordatirarediseases.com.

PRINCIPAL DISPLAY PANEL - 180 Gram Bottle Label

NDC 52276-400-01

Cystadane®
betaine anhydrous
for oral solution

180 grams

1 gram of betaine anhydrous
powder per scoopful

RECORDATI
RARE DISEASES
Rx only